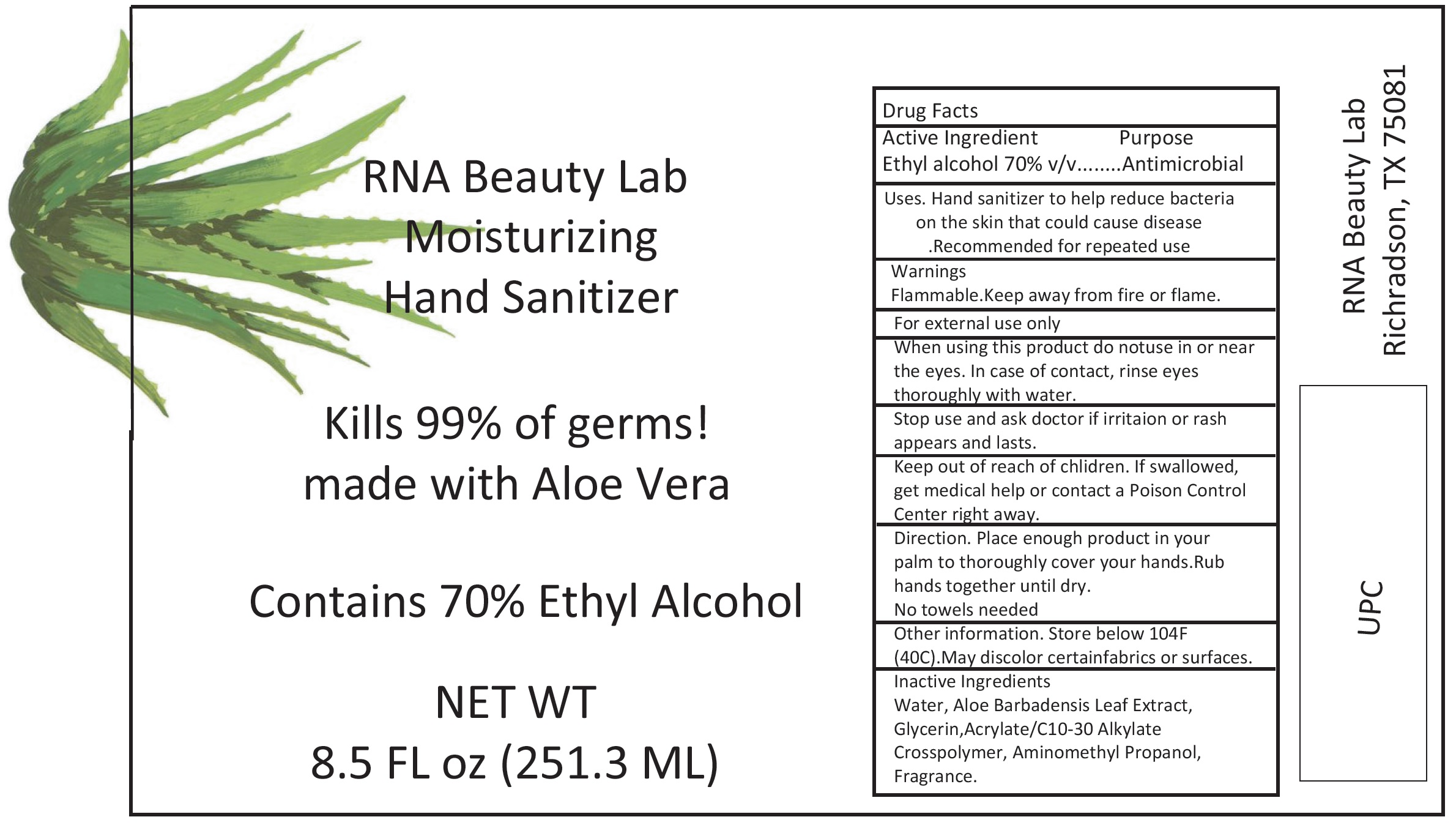 DRUG LABEL: RNA Beauty Lab Moisturizing Hand Sanitizer
NDC: 79801-000 | Form: GEL
Manufacturer: Rna Beauty Labs LLC
Category: otc | Type: HUMAN OTC DRUG LABEL
Date: 20200806

ACTIVE INGREDIENTS: ALCOHOL 0.7 mL/1 mL
INACTIVE INGREDIENTS: WATER; ALOE VERA LEAF; GLYCERIN; AMINOMETHYLPROPANOL

RNA Beauty Lab Moisturizing Hand Sanitizer

Active Ingredient

Ethyl alcohol 70% v/v

Purpose

Antimicrobial

Uses.

Hand sanitizer to help reduce bacteria on the skin that could cause disease .Recommended for repeated use

Warnings

Flammable.Keep away from fire or flame. For external use only

When using this product

do notuse in or near the eyes. In case of contact, rinse eyes thoroughly with water.

Stop use and ask doctor

if irritaion or rash appears and lasts.

Keep out of reach of chlidren.

If swallowed, get medical help or contact a Poison Control Center right away.

Direction.

Place enough product in your palm to thoroughly cover your hands.Rub hands together until dry. No towels needed

Other information.

Store below 104F (40C).May discolor certainfabrics or surfaces.

Inactive Ingredients

Water, Aloe Barbadensis Leaf Extract, Glycerin,Acrylate/C10-30 Alkylate Crosspolymer, Aminomethyl Propanol, Fragrance.